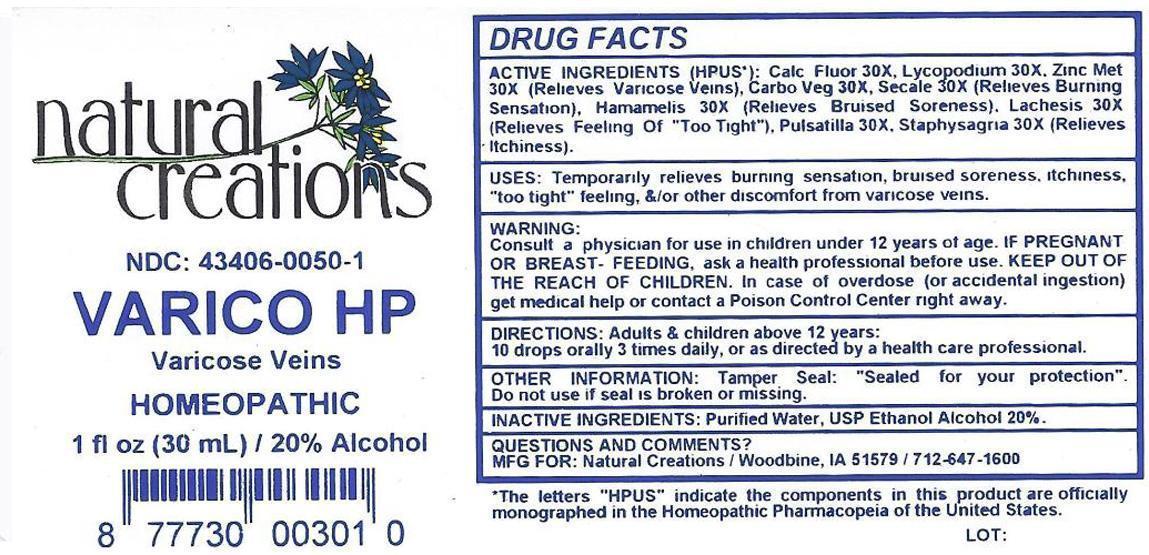 DRUG LABEL: Varico HP
NDC: 43406-0050 | Form: LIQUID
Manufacturer: Natural Creations, Inc.
Category: homeopathic | Type: HUMAN OTC DRUG LABEL
Date: 20130103

ACTIVE INGREDIENTS: CALCIUM FLUORIDE 30 [hp_X]/1 mL; ACTIVATED CHARCOAL 30 [hp_X]/1 mL; HAMAMELIS VIRGINIANA ROOT BARK/STEM BARK 30 [hp_X]/1 mL; LACHESIS MUTA VENOM 30 [hp_X]/1 mL; LYCOPODIUM CLAVATUM SPORE 30 [hp_X]/1 mL; PULSATILLA VULGARIS 30 [hp_X]/1 mL; CLAVICEPS PURPUREA SCLEROTIUM 30 [hp_X]/1 mL; DELPHINIUM STAPHISAGRIA SEED 30 [hp_X]/1 mL; ZINC 30 [hp_X]/1 mL
INACTIVE INGREDIENTS: WATER; ALCOHOL

Varico HP

ACTIVE INGREDIENT

ACTIVE INGREDIENTS (HPUS*): Calcarea Fluorica 30X, Carbo Vegetabilis 30X, Hamamelis Virginiana 30X, Lachesis Mutus 30X, Lycopodium Clavatum 30X, Pulsatilla 30X, Secale Cornutum 30X, Staphysagria 30X, Zincum Metallicum 30X

INDICATIONS AND USAGE

USES: Temporarily relieves burning sensation, bruised soreness, itchiness, "too tight" feeling, &/or other discomfort from varicose veins.

WARNING:

Consult a physician for use in children under 12 years or age. IF PREGNANT OR BREAST-FEEDING, ask a health care professional before use. KEEP OUT OF THE REACH OF CHILDREN. In case of overdose (or accidental ingestion) get medical help or contact a Poison Control Center right away.

DOSAGE AND ADMINISTRATION

DIRECTIONS: Adults and children above 12 years: 10 drops orally 3 times daily, or as directed by a health care professional.

OTHER INFORMATION: Tamper Seal: "Sealed for your protection."

Do not use if seal is broken or missing.

REFERENCES

*The letters "HPUS" indicate the components in the product are officially monographed in the Homeopathic Pharmacopeia of the United States.

INACTIVE INGREDIENTS: Purified Water, USP Ethanol Alcohol 20%

QUESTIONS AND COMMENTS?

MFG FOR: Natural Creations / Woodbine, IA / 51579 712.647.1600

LOT:

PURPOSE

USES: Temporarily relieves burning sensation, bruised soreness, itchiness, "too tight" feeling, &/or other discomfort from varicose veins.

KEEP OUT OF REACH OF CHILDREN

KEEP OUT OF THE REACH OF CHILDREN. In case of overdose (or accidental ingestion) get medical help or contact a Poison Control Center.

PACKAGE LABEL

NDC: 43406-0050-1

VARICO HP

Varicose Veins

HOMEOPATHIC

1 fl oz (30 mL) / 20% Alcohol

UPC: 877730003010